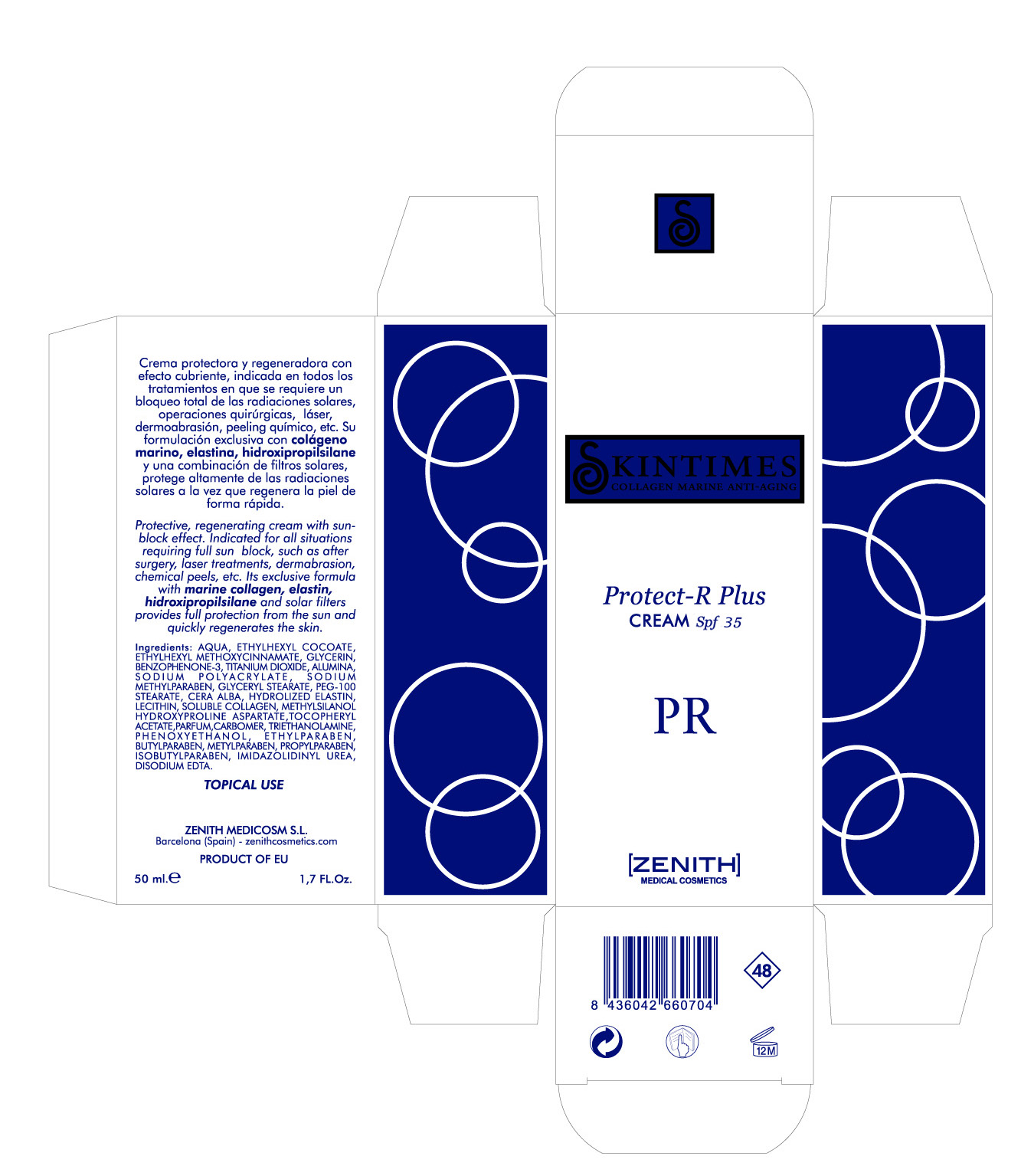 DRUG LABEL: Protector
NDC: 42248-127 | Form: CREAM
Manufacturer: Zenith Medicosm SL
Category: otc | Type: HUMAN OTC DRUG LABEL
Date: 20120221

ACTIVE INGREDIENTS: OCTINOXATE 3.75 mL/50 mL; TITANIUM DIOXIDE 12.5 mL/50 mL; OXYBENZONE 3 mL/50 mL
INACTIVE INGREDIENTS: ALUMINUM OXIDE; PROPYLPARABEN; ALPHA-TOCOPHEROL ACETATE; SODIUM COCOYL ISETHIONATE; SODIUM POLYACRYLATE (8000 MW); METHYLPARABEN SODIUM; WATER; GLYCERYL MONOSTEARATE; PEG-100 STEARATE; WHITE WAX; HYDROGENATED SOYBEAN LECITHIN; GLYCERIN; TROLAMINE; ISOBUTYLPARABEN; HYDROLYZED ELASTIN, BOVINE, ALKALINE (1000 MW); CARBOMER 934; IMIDUREA; EDETATE DISODIUM; METHYLPARABEN; COLLAGEN, SOLUBLE, FISH SKIN; PHENOXYETHANOL; BUTYLPARABEN; ETHYLPARABEN; (2-CARBETHOXYETHYL)DIETHOXY(METHYL)SILANE; HYDROXYPROLINE; ASPARTIC ACID

Drug Facts

Active Ingredient

Octinoxate 7.5%

Titanium Dioxide 25%

Oxybenzone 6%

Description

Made with plant squalene, marine collagen and hyaluronic acid, intensive cream with double moisturizing control provides an overall reduction of signs of ageing by progressively activating natural defence mechanisms. It strenghtens the moisture barrier and favours the skin regeneration process. Suitable for use on very dry, dehydrated skin with wrinkles and lack of elasticity.

50ml. 1.7 fl. Oz

Warning

TOPICAL USE